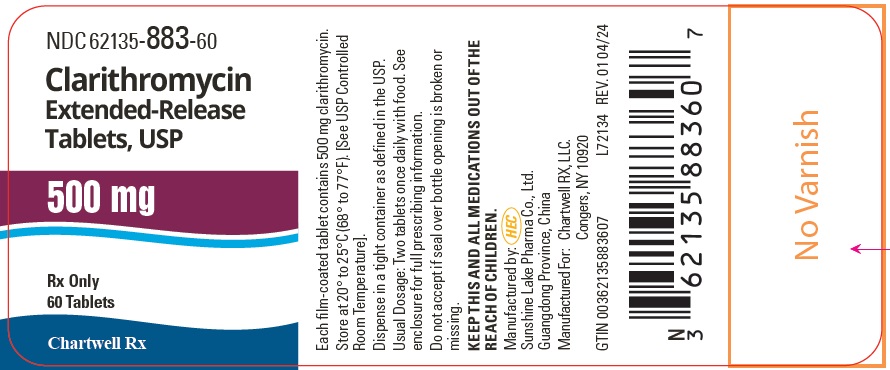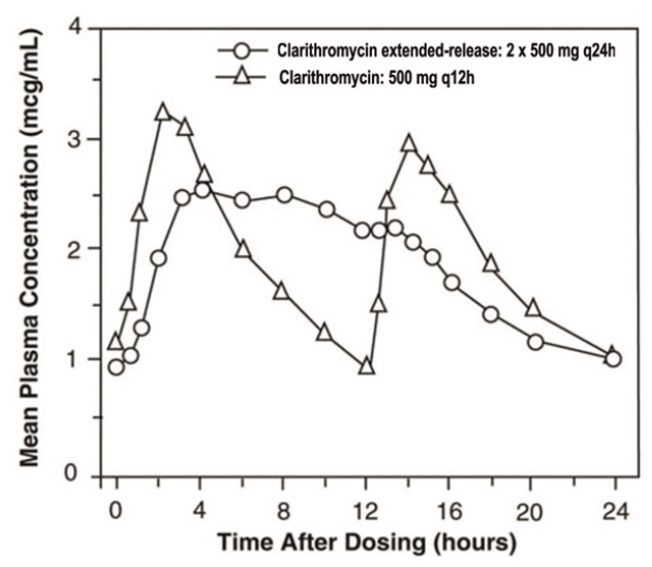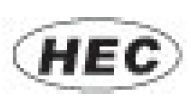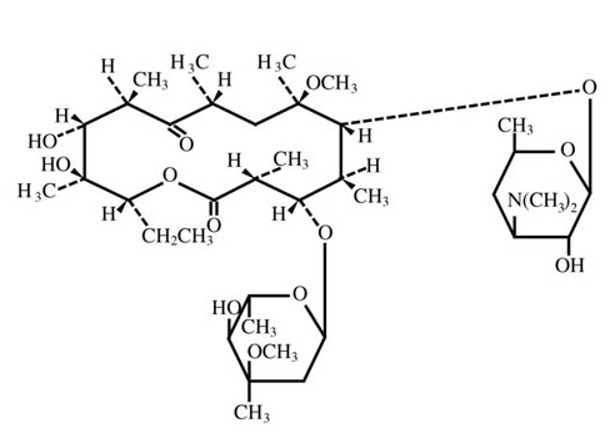 DRUG LABEL: CLARITHROMYCIN
NDC: 62135-883 | Form: TABLET, FILM COATED, EXTENDED RELEASE
Manufacturer: Chartwell RX, LLC
Category: prescription | Type: HUMAN PRESCRIPTION DRUG LABEL
Date: 20251210

ACTIVE INGREDIENTS: CLARITHROMYCIN 500 mg/1 1
INACTIVE INGREDIENTS: GLYCERYL DIBEHENATE; HYPROMELLOSES; LACTOSE MONOHYDRATE; MAGNESIUM STEARATE; POLYETHYLENE GLYCOL, UNSPECIFIED; TITANIUM DIOXIDE

HIGHLIGHTS OF PRESCRIBING INFORMATION

Clarithromycin Extended-Release Tablets, USP
These highlights do not include all the information needed to use CLARITHROMYCIN EXTENDED-RELEASE TABLETS safely and effectively. See full prescribing information for CLARITHROMYCIN EXTENDED-RELEASE TABLETS.
CLARITHROMYCIN extended-release tablets, for oral use
Initial U.S. Approval: 1991

RECENT MAJOR CHANGES

Contraindications (4) 5/2023

Drug Interactions (7) 5/2023

1 INDICATIONS AND USAGE

Clarithromycin extended-release tablets is a macrolide antimicrobial indicated for mild to moderate infections caused by designated, susceptible bacteria in the following:

- Acute Bacterial Exacerbation of Chronic Bronchitis in Adults (1.1)
- Acute Maxillary Sinusitis (1.2)
- Community-Acquired Pneumonia (1.3)

Limitations of Use

Clarithromycin extended-release tablets are indicated only for acute bacterial exacerbation of chronic bronchitis, acute maxillary sinusitis, and community-acquired pneumonia in adults. (1.9)

To reduce the development of drug-resistant bacteria and maintain the effectiveness of clarithromycin extended-release tablets and other antibacterial drugs, clarithromycin extended-release tablets should be used only to treat or prevent infections that are proven or strongly suspected to be caused by bacteria. (1.9)

2 DOSAGE AND ADMINISTRATION

- Adults: clarithromycin extended-release tablets 1 gram every 24 hours for 7–14 days (2.2)
- Reduce dose in moderate renal impairment with concomitant atazanavir or ritonavir-containing regimens and in severe renal impairment (2.6)

3 DOSAGE FORMS AND STRENGTHS

- Extended-release Tablets: 500 mg (3)

4 CONTRAINDICATIONS

- Hypersensitivity to clarithromycin or any macrolide drug (4.1)
- Cisapride and pimozide (4.2)
- History of cholestatic jaundice/hepatic dysfunction with use of clarithromycin (4.3)
- Colchicine in renal or hepatic impairment (4.4)
- Lomitapide, lovastatin, and simvastatin (4.5)
- Ergot alkaloids (ergotamine or dihydroergotamine) (4.6)
- Lurasidone (4.7)

5 WARNINGS AND PRECAUTIONS

- Severe Acute Hypersensitivity Reactions: Discontinue clarithromycin if occurs (5.1)
- QT Prolongation: Avoid clarithromycin in patients with known QT prolongation or receiving drugs known to prolong the QT interval, ventricular arrhythmia (torsades de pointes), hypokalemia/hypomagnesemia, significant bradycardia, or taking Class IA or III antiarrhythmics (5.2)
- Hepatotoxicity: Discontinue if signs and symptoms of hepatitis occur (5.3)
- Serious adverse reactions can occur due to drug interactions of clarithromycin with colchicine, some lipid-lowering agents, some calcium channel blockers, and other drugs (5.4)
- Risk of all-cause mortality one year or more after the end of treatment in patients with coronary artery disease. Balance this potential risk with the treatment benefits when prescribing clarithromycin tablets in these patients. (5.5)
- Clostridium difficileassociated diarrhea (CDAD): Evaluate if diarrhea occurs (5.6)
- Embryo-Fetal Toxicity: Based on animal findings, clarithromycin is not recommended for use in pregnant women except in clinical circumstances where no alternative therapy is appropriate (5.7)
- Exacerbation of myasthenia gravis has been reported in patients receiving clarithromycin therapy. (5.8)

6 ADVERSE REACTIONS

- Most frequent adverse reactions for both adult and pediatric populations in clinical trials: abdominal pain, diarrhea, nausea, vomiting, dysgeusia (6.1)

To report SUSPECTED ADVERSE REACTIONS, contact Chartwell RX, LLC. at 1-845-232-1683 or FDA at 1-800-FDA-1088 or www.fda.gov/medwatch.

7 DRUG INTERACTIONS

- Co-administration of clarithromycin can alter the concentrations of other drugs. The potential for drug-drug interactions must be considered prior to and during therapy. (4, 5.2, 5.4, 7)

8 USE IN SPECIFIC POPULATIONS

- Geriatric: Increased risk of torsades de pointes(8.5)

FULL PRESCRIBING INFORMATION

1 INDICATIONS AND USAGE

1.1 Acute Bacterial Exacerbation of Chronic Bronchitis

Clarithromycin extended-release tablets are indicated in adults for the treatment of mild to moderate infections caused by susceptible isolates due to Haemophilus influenzae, Haemophilus parainfluenzae, Moraxella catarrhalis,or Streptococcus pneumoniae [see Indications and Usage (1.9)].

1.2 Acute Maxillary Sinusitis

Clarithromycin extended-release tablets (in adults) are indicated for the treatment of mild to moderate infections caused by susceptible isolates due to Haemophilus influenzae, Moraxella catarrhalis,or Streptococcus pneumoniae [see Indications and Usage (1.9)].

1.3 Community-Acquired Pneumonia

Clarithromycin extended-release tablets are indicated [see Indications and Usage (1.9)] for the treatment of mild to moderate infections caused by susceptible isolates due to:

- Haemophilus influenzae(in adults)
- Haemophilus parainfluenzae(in adults)
- Moraxella catarrhalis(in adults)
- Mycoplasma pneumoniae, Streptococcus pneumoniae, Chlamydophila pneumoniae(in adults)

1.9 Limitations of Use

Clarithromycin extended-release tablets are indicated only for acute maxillary sinusitis, acute bacterial exacerbation of chronic bronchitis, and community-acquired pneumonia in adults. The efficacy and safety of clarithromycin extended-release tablets in treating other infections for which clarithromycin immediate release tablets and clarithromycin granules are approved have not been established.

There is resistance to macrolides in certain bacterial infections caused by Streptococcus pneumoniaeand Staphylococcus aureus. Susceptibility testing should be performed when clinically indicated.

1.10 Usage

To reduce the development of drug-resistant bacteria and maintain the effectiveness of clarithromycin extended-release tablets and other antibacterial drugs, clarithromycin extended-release tablets should be used only to treat or prevent infections that are proven or strongly suspected to be caused by susceptible bacteria. When culture and susceptibility information are available, they should be considered in selecting or modifying antibacterial therapy. In the absence of such data, local epidemiology and susceptibility patterns may contribute to the empiric selection of therapy.

2 DOSAGE AND ADMINISTRATION

2.1 Important Administration Instructions

Clarithromycin extended-release tablets should be taken with food. Swallow clarithromycin extended-release tablets whole; do not chew, break or crush clarithromycin extended-release tablets.

2.2 Adult Dosage

The recommended dosages of clarithromycin extended-release tablets for the treatment of mild to moderate infections in adults are listed in Table 1.

Table 1. Adult Dosage Guidelines
 | Clarithromycin Extended-release Tablets
Infection | Dosage (every 24 hours) | Duration (days)
Acute bacterial exacerbation of chronic bronchitis | 1 gram | 7
Acute maxillary sinusitis | 1 gram | 14
Community-acquired pneumonia | 1 gram | 7

2.6 Dosage Adjustment in Patients with Renal Impairment

See Table 2 for dosage adjustment in patients with moderate or severe renal impairment with or without concomitant atazanavir or ritonavir-containing regimens [see Drug Interactions (7)] .

Table 2. Clarithromycin Dosage Adjustments in Patients with Renal Impairment
 | Recommended Clarithromycin Dosage Reduction
Patients with severe renal impairment (CL crof <30 mL/min) | Reduce the dosage of clarithromycin by 50%
Patients with moderate renal impairment (CL crof 30 to 60 mL/min) taking concomitant atazanavir or ritonavir-containing regimens | Reduce the dosage of clarithromycin by 50%
Patients with severe renal impairment (CL crof <30 mL/min) taking concomitant atazanavir or ritonavir-containing regimens | Reduce the dosage of clarithromycin by 75%

2.7 Dosage Adjustment Due to Drug Interactions

Decrease the dose of clarithromycin by 50 % when co-administered with atazanavir [see Drug Interactions (7)] . Dosage adjustments for other drugs when co-administered with clarithromycin may be recommended due to drug interactions [see Drug Interactions (7)] .

3 DOSAGE FORMS AND STRENGTHS

Clarithromycin Extended-Release Tablets, USP are supplied as white or off-white, capsular-shaped film-coated 500 mg tablets debossed “S58” on one side and blank on the other side.

4 CONTRAINDICATIONS

4.1 Hypersensitivity

Clarithromycin is contraindicated in patients with a known hypersensitivity to clarithromycin, erythromycin, or any of the macrolide antibacterial drugs [see Warnings and Precautions (5.1)] .

4.2 Cisapride and Pimozide

Concomitant administration of clarithromycin with cisapride and pimozide is contraindicated [see Drug Interactions (7)] .

There have been postmarketing reports of drug interactions when clarithromycin is co-administered with cisapride or pimozide, resulting in cardiac arrhythmias (QT prolongation, ventricular tachycardia, ventricular fibrillation, and torsades de pointes) most likely due to inhibition of metabolism of these drugs by clarithromycin. Fatalities have been reported.

4.3 Cholestatic Jaundice/Hepatic Dysfunction

Clarithromycin is contraindicated in patients with a history of cholestatic jaundice or hepatic dysfunction associated with prior use of clarithromycin.

4.4 Colchicine

Concomitant administration of clarithromycin and colchicine is contraindicated in patients with renal or hepatic impairment.

4.5 Lomitapide, Lovastatin, and Simvastatin

Concomitant administration of clarithromycin with lomitapide is contraindicated due to potential for markedly increased transaminases [see Warnings and Precautions (5.4)and Drug Interactions (7)].

Concomitant administration of clarithromycin with HMG-CoA reductase inhibitors (statins) that are extensively metabolized by CYP3A4 (lovastatin or simvastatin) is contraindicated, due to the increased risk of myopathy, including rhabdomyolysis [see Warnings and Precautions (5.4)and Drug Interactions (7)].

4.6 Ergot Alkaloids

Concomitant administration of clarithromycin and ergotamine or dihydroergotamine is contraindicated [see Drug Interactions (7)].

4.7 Lurasidone

Concomitant administration of clarithromycin and lurasidone is contraindicated since it may result in an increase in lurasidone exposure and the potential for serious adverse reactions [see Drug Interactions (7)] .

4.8 Contraindications for Co-administered Drugs

For information about contraindications of other drugs indicated in combination with clarithromycin, refer to their full prescribing information (contraindications section).

5 WARNINGS AND PRECAUTIONS

5.1 Severe Acute Hypersensitivity Reactions

In the event of severe acute hypersensitivity reactions, such as anaphylaxis, Stevens-Johnson Syndrome, toxic epidermal necrolysis, drug rash with eosinophilia and systemic symptoms (DRESS), Henoch-Schonlein purpura, and acute generalized exanthematous pustulosis, discontinue clarithromycin therapy immediately and institute appropriate treatment.

5.2 QT Prolongation

- Clarithromycin has been associated with prolongation of the QT interval and infrequent cases of arrhythmia. Cases of torsades de pointeshave been spontaneously reported during postmarketing surveillance in patients receiving clarithromycin. Fatalities have been reported.

Avoid clarithromycin in the following patients:

- patients with known prolongation of the QT interval, ventricular cardiac arrhythmia, including torsades de pointes
- patients receiving drugs known to prolong the QT interval [see also Contraindications (4.2)]
- patients with ongoing proarrhythmic conditions such as uncorrected hypokalemia or hypomagnesemia, clinically significant bradycardia and in patients receiving Class IA (e.g., quinidine, procainamide, disopyramide) or Class III (e.g., dofetilide, amiodarone, sotalol) antiarrhythmic agents.

Elderly patients may be more susceptible to drug-associated effects on the QT interval [see Use in Specific Populations (8.5)].

5.3 Hepatotoxicity

Hepatic dysfunction, including increased liver enzymes, and hepatocellular and/or cholestatic hepatitis, with or without jaundice, has been reported with clarithromycin. This hepatic dysfunction may be severe and is usually reversible. In some instances, hepatic failure with fatal outcome has been reported and generally has been associated with serious underlying diseases and/or concomitant medications. Symptoms of hepatitis can include anorexia, jaundice, dark urine, pruritus, or tender abdomen. Discontinue clarithromycin immediately if signs and symptoms of hepatitis occur.

5.4 Serious Adverse Reactions Due to Concomitant Use with Other Drugs

Drugs metabolized by CYP3A4: Serious adverse reactions have been reported in patients taking clarithromycin concomitantly with CYP3A4 substrates. These include colchicine toxicity with colchicine; markedly increased transaminases with lomitapide; rhabdomyolysis with simvastatin, lovastatin, and atorvastatin; hypoglycemia and cardiac arrhythmias (e.g., torsades de pointes) with disopyramide; and hypotension and acute kidney injury with calcium channel blockers metabolized by CYP3A4 (e.g., verapamil, amlodipine, diltiazem, nifedipine). Most reports of acute kidney injury with calcium channel blockers metabolized by CYP3A4 involved elderly patients 65 years of age or older. Use clarithromycin with caution when administered concurrently with medications that induce the cytochrome CYP3A4 enzyme. The use of clarithromycin with lomitapide, simvastatin, lovastatin, ergotamine, or dihydroergotamine is contraindicated [see Contraindications (4.5, 4.6) and Drug Interactions (7)].

Colchicine: Life-threatening and fatal drug interactions have been reported in patients treated with clarithromycin and colchicine. Clarithromycin is a strong CYP3A4 inhibitor and this interaction may occur while using both drugs at their recommended doses. If co-administration of clarithromycin and colchicine is necessary in patients with normal renal and hepatic function, reduce the dose of colchicine. Monitor patients for clinical symptoms of colchicine toxicity. Concomitant administration of clarithromycin and colchicine is contraindicated in patients with renal or hepatic impairment [see Contraindications (4.4)and Drug Interactions (7)].

Lomitapide: Concomitant use of clarithromycin with lomitapide is contraindicated [see Contraindications (4.5)] . Lomitapide is metabolized by CYP3A4, and concomitant treatment with clarithromycin increases the plasma concentration of lomitapide, which increases the risk of elevation in transaminases [see Drug Interactions (7)] . If treatment with clarithromycin cannot be avoided, therapy with lomitapide must be suspended during the course of treatment.

HMG-CoA Reductase Inhibitors (statins): Concomitant use of clarithromycin with lovastatin or simvastatin is contraindicated [see Contraindications (4.5)] as these statins are extensively metabolized by CYP3A4, and concomitant treatment with clarithromycin increases their plasma concentration, which increases the risk of myopathy, including rhabdomyolysis. Cases of rhabdomyolysis have been reported in patients taking clarithromycin concomitantly with these statins. If treatment with clarithromycin cannot be avoided, therapy with lovastatin or simvastatin must be suspended during the course of treatment.

Exercise caution when prescribing clarithromycin with atorvastatin or pravastatin. In situations where the concomitant use of clarithromycin with atorvastatin or pravastatin cannot be avoided, atorvastatin dose should not exceed 20 mg daily and pravastatin dose should not exceed 40 mg daily. Use of a statin that is not dependent on CYP3A metabolism (e.g. fluvastatin) can be considered. It is recommended to prescribe the lowest registered dose if concomitant use cannot be avoided.

Oral Hypoglycemic Agents/Insulin: The concomitant use of clarithromycin and oral hypoglycemic agents and/or insulin can result in significant hypoglycemia. With certain hypoglycemic drugs such as nateglinide, pioglitazone, repaglinide and rosiglitazone, inhibition of CYP3A enzyme by clarithromycin may be involved and could cause hypoglycemia when used concomitantly. Careful monitoring of glucose is recommended [see Drug Interactions (7)].

Quetiapine: Use quetiapine and clarithromycin concomitantly with caution. Co-administration could result in increased quetiapine exposure and quetiapine related toxicities such as somnolence, orthostatic hypotension, altered state of consciousness, neuroleptic malignant syndrome, and QT prolongation. Refer to quetiapine prescribing information for recommendations on dose reduction if co-administered with CYP3A4 inhibitors such as clarithromycin [see Drug Interactions (7)].

Oral Anticoagulants: There is a risk of serious hemorrhage and significant elevations in INR and prothrombin time when clarithromycin is co-administered with warfarin. Monitor INR and prothrombin times frequently while patients are receiving clarithromycin and oral anticoagulants concurrently [see Drug Interactions (7)].

Benzodiazepines: Increased sedation and prolongation of sedation have been reported with concomitant administration of clarithromycin and triazolobenzodiazepines, such as triazolam and midazolam [see Drug Interactions (7)].

5.5 All-Cause Mortality in Patients With Coronary Artery Disease 1 to 10 Years After Clarithromycin Exposure

In one clinical trial evaluating treatment with clarithromycin on outcomes in patients with coronary artery disease, an increase in risk of all-cause mortality one year or more after the end of treatment was observed in patients randomized to receive clarithromycin.^1Clarithromycin for treatment of coronary artery disease is not an approved indication. The cause of the increased risk has not been established. Other epidemiologic studies evaluating this risk have shown variable results [see Adverse Reactions (6.1)] . Consider balancing this potential risk with the treatment benefits when prescribing clarithromycin in patients who have suspected or confirmed coronary artery disease.

5.6 Clostridium difficileAssociated Diarrhea

Clostridium difficileAssociated Diarrhea (CDAD) has been reported with use of nearly all antibacterial agents, including clarithromycin, and may range in severity from mild diarrhea to fatal colitis. Treatment with antibacterial agents alters the normal flora of the colon leading to overgrowth of C. difficile.

C. difficileproduces toxins A and B which contribute to the development of CDAD. Hypertoxin producing strains of C. difficilecause increased morbidity and mortality, as these infections can be refractory to antimicrobial therapy and may require colectomy. CDAD must be considered in all patients who present with diarrhea following antibacterial use. Careful medical history is necessary since CDAD has been reported to occur over two months after the administration of antibacterial agents.

If CDAD is suspected or confirmed, ongoing antibacterial use not directed against C. difficilemay need to be discontinued. Appropriate fluid and electrolyte management, protein supplementation, antibacterial treatment of C. difficile, and surgical evaluation should be instituted as clinically indicated.

5.7 Embryo-Fetal Toxicity

Based on findings from animal studies, clarithromycin is not recommended for use in pregnant women except in clinical circumstances where no alternative therapy is appropriate. If clarithromycin is used during pregnancy, or if pregnancy occurs while the patient is taking this drug, the patient should be apprised of the potential hazard to the fetus. Clarithromycin demonstrated adverse effects on pregnancy outcome and/or embryo fetal development, including fetal malformations, in pregnant animals administered oral clarithromycin [see Use in Specific Populations (8.1)].

5.8 Exacerbation of Myasthenia Gravis

Exacerbation of symptoms of myasthenia gravis and new onset of symptoms of myasthenic syndrome has been reported in patients receiving clarithromycin therapy.

5.9 Development of Drug Resistant Bacteria

Prescribing clarithromycin in the absence of a proven or strongly suspected bacterial infection or a prophylactic indication is unlikely to provide benefit to the patient and increases the risk of the development of drug-resistant bacteria.

6 ADVERSE REACTIONS

The following serious adverse reactions are described below and elsewhere in the labeling:

- Acute Hypersensitivity Reactions [see Warnings and Precautions (5.1)]
- QT Prolongation [see Warnings and Precautions (5.2)]
- Hepatotoxicity [see Warnings and Precautions (5.3)]
- Serious Adverse Reactions Due to Concomitant Use with Other Drugs [see Warnings and Precautions (5.4)]
- Clostridium difficileAssociated Diarrhea [see Warnings and Precautions (5.6)]
- Exacerbation of Myasthenia Gravis [see Warnings and Precautions (5.8)]

6.1 Clinical Trials Experience

Because clinical studies are conducted under widely varying conditions, adverse reaction rates observed in the clinical studies of a drug cannot be directly compared to rates in the clinical studies of another drug and may not reflect the rates observed in practice.

Based on pooled data across all indications, the most frequent adverse reactions for both adult and pediatric populations observed in clinical trials are abdominal pain, diarrhea, nausea, vomiting and dysgeusia. Also reported were dyspepsia, liver function test abnormal, anaphylactic reaction, candidiasis, headache, insomnia, and rash.

Less Frequent Adverse Reactions Observed During Clinical Trials of Clarithromycin

Based on pooled data across all indications, the following adverse reactions were observed in clinical trials with clarithromycin at a rate less than 1%:

Blood and Lymphatic System Disorders: Leukopenia, neutropenia, thrombocythemia, eosinophilia

Cardiac Disorders: Electrocardiogram QT prolonged, cardiac arrest, atrial fibrillation, extrasystoles, palpitations

Ear and Labyrinth Disorders: Vertigo, tinnitus, hearing impaired

Gastrointestinal Disorders: Stomatitis, glossitis, esophagitis, gastrooesophageal reflux disease, gastritis, proctalgia, abdominal distension, constipation, dry mouth, eructation, flatulence

General Disorders and Administration Site Conditions: Malaise, pyrexia, asthenia, chest pain, chills, fatigue

Hepatobiliary Disorders: Cholestasis, hepatitis

Immune System Disorders: Hypersensitivity

Infections and Infestations: Cellulitis, gastroenteritis, infection, vaginal infection

Investigations: Blood bilirubin increased, blood alkaline phosphatase increased, blood lactate dehydrogenase increased, albumin globulin ratio abnormal

Metabolism and Nutrition Disorders: Anorexia, decreased appetite

Musculoskeletal and Connective Tissue Disorders: Myalgia, muscle spasms, nuchal rigidity

Nervous System Disorders: Dizziness, tremor, loss of consciousness, dyskinesia, somnolence

Psychiatric Disorders: Anxiety, nervousness

Renal and Urinary Disorders: Blood creatinine increased, blood urea increased

Respiratory, Thoracic and Mediastinal Disorders: Asthma, epistaxis, pulmonary embolism

Skin and Subcutaneous Tissue Disorders: Urticaria, dermatitis bullous, pruritus, hyperhidrosis, rash maculo-papular

Gastrointestinal Adverse Reactions

In the acute exacerbation of chronic bronchitis and acute maxillary sinusitis studies overall gastrointestinal adverse reactions were reported by a similar proportion of patients taking either clarithromycin tablets or clarithromycin extended-release tablets; however, patients taking clarithromycin extended-release tablets reported significantly less severe gastrointestinal symptoms compared to patients taking clarithromycin tablets. In addition, patients taking clarithromycin extended-release tablets had significantly fewer premature discontinuations for drug-related gastrointestinal or abnormal taste adverse reactions compared to clarithromycin immediate-release tablets.

All-Cause Mortality in Patients with Coronary Artery Disease 1 to 10 Years Following Clarithromycin Exposure

In one clinical trial evaluating treatment with clarithromycin on outcomes in patients with coronary artery disease, an increase in risk of all-cause mortality was observed in patients randomized to clarithromycin. Clarithromycin for treatment of coronary artery disease is not an approved indication. Patients were treated with clarithromycin or placebo for 14 days and observed for primary outcome events (e.g., all-cause mortality or non-fatal cardiac events) for several years. 1A numerically higher number of primary outcome events in patients randomized to receive clarithromycin was observed with a hazard ratio of 1.06 (95% confidence interval 0.98 to 1.14). However, at follow-up 10 years post-treatment, there were 866 (40%) deaths in the clarithromycin group and 815 (37%) deaths in the placebo group that represented a hazard ratio for all-cause mortality of 1.10 (95% confidence interval 1.00 to 1.21). The difference in the number of deaths emerged after one year or more after the end of treatment.

The cause of the difference in all-cause mortality has not been established. Other epidemiologic studies evaluating this risk have shown variable results [see Warnings and Precautions (5.5)].

6.2 Postmarketing Experience

The following adverse reactions have been identified during post-approval use of clarithromycin. Because these reactions are reported voluntarily from a population of uncertain size, it is not always possible to reliably estimate their frequency or establish a causal relationship to drug exposure.

Blood and Lymphatic System: Thrombocytopenia, agranulocytosis

Cardiac: Ventricular arrhythmia, ventricular tachycardia, torsades de pointes

Ear and Labyrinth: Deafness was reported chiefly in elderly women and was usually reversible.

Gastrointestinal: Pancreatitis acute, tongue discoloration, tooth discoloration was reported and was usually reversible with professional cleaning upon discontinuation of the drug.

There have been reports of clarithromycin extended-release tablets in the stool, many of which have occurred in patients with anatomic (including ileostomy or colostomy) or functional gastrointestinal disorders with shortened GI transit times. In several reports, tablet residues have occurred in the context of diarrhea. It is recommended that patients who experience tablet residue in the stool and no improvement in their condition should be switched to a different clarithromycin formulation (e.g. suspension) or another antibacterial drug.

Hepatobiliary: Hepatic failure, jaundice hepatocellular. Adverse reactions related to hepatic dysfunction have been reported with clarithromycin [see Warnings and Precautions (5.2)].

Infections and Infestations: Pseudomembranous colitis [see Warnings and Precautions (5.6)]

Immune System: Anaphylactic reactions, angioedema

Investigations: Prothrombin time prolonged, white blood cell count decreased, international normalized ratio increased. Abnormal urine color has been reported, associated with hepatic failure.

Metabolism and Nutrition: Hypoglycemia has been reported in patients taking oral hypoglycemic agents or insulin.

Musculoskeletal and Connective Tissue: Myopathy rhabdomyolysis was reported and in some of the reports, clarithromycin was administered concomitantly with statins, fibrates, colchicine or allopurinol [see Contraindications (4.5)and Warnings and Precautions (5.4)] .

Nervous System: Parosmia, anosmia, ageusia, paresthesia and convulsions

Psychiatric: Abnormal behavior, confusional state, depersonalization, disorientation, hallucination, depression, manic behavior, abnormal dream, psychotic disorder. These disorders usually resolve upon discontinuation of the drug.

Renal and Urinary: Nephritis interstitial, renal failure

Skin and Subcutaneous Tissue: Stevens-Johnson syndrome, toxic epidermal necrolysis, drug rash with eosinophilia and systemic symptoms (DRESS), Henoch-Schonlein purpura, acne, acute generalized exanthematous pustulosis

Vascular: Hemorrhage

7 DRUG INTERACTIONS

Co-administration of clarithromycin is known to inhibit CYP3A, and a drug primarily metabolized by CYP3A may be associated with elevations in drug concentrations that could increase or prolong both therapeutic and adverse effects of the concomitant drug.

Clarithromycin should be used with caution in patients receiving treatment with other drugs known to be CYP3A enzyme substrates, especially if the CYP3A substrate has a narrow safety margin (e.g., carbamazepine) and/or the substrate is extensively metabolized by this enzyme. Adjust dosage when appropriate and monitor serum concentrations of drugs primarily metabolized by CYP3A closely in patients concurrently receiving clarithromycin.

Table 8: Clinically Significant Drug Interactions with Clarithromycin
Drugs That Are Affected By Clarithromycin
Drug(s) with Pharmacokinetics Affected by Clarithromycin | Recommendation | Comments
Antiarrhythmics:
Disopyramide Quinidine Dofetilide Amiodarone Sotalol Procainamide | Not Recommended | Disopyramide, Quinidine: There have been postmarketing reports of torsades de pointesoccurring with concurrent use of clarithromycin and quinidine or disopyramide. Electrocardiograms should be monitored for QTc prolongation during coadministration of clarithromycin with these drugs [see Warnings and Precautions (5.3)]. Serum concentrations of these medications should also be monitored. There have been spontaneous or published reports of CYP3A based interactions of clarithromycin with disopyramide and quinidine. There have been postmarketing reports of hypoglycemia with the concomitant administration of clarithromycin and disopyramide. Therefore, blood glucose levels should be monitored during concomitant administration of clarithromycin and disopyramide.
Digoxin | Use With Caution | Digoxin: Digoxin is a substrate for P-glycoprotein (Pgp) and clarithromycin is known to inhibit Pgp. When clarithromycin and digoxin are co-administered, inhibition of Pgp by clarithromycin may lead to increased exposure of digoxin. Elevated digoxin serum concentrations in patients receiving clarithromycin and digoxin concomitantly have been reported in postmarketing surveillance. Some patients have shown clinical signs consistent with digoxin toxicity, including potentially fatal arrhythmias. Monitoring of serum digoxin concentrations should be considered, especially for patients with digoxin concentrations in the upper therapeutic range.
Oral Anticoagulants:
Warfarin | Use With Caution | Oral anticoagulants: Spontaneous reports in the postmarketing period suggest that concomitant administration of clarithromycin and oral anticoagulants may potentiate the effects of the oral anticoagulants. Prothrombin times should be carefully monitored while patients are receiving clarithromycin and oral anticoagulants simultaneously [see Warnings and Precautions (5.4)].
Antiepileptics:
Carbamazepine | Use With Caution | Carbamazepine: Concomitant administration of single doses of clarithromycin and carbamazepine has been shown to result in increased plasma concentrations of carbamazepine. Blood level monitoring of carbamazepine may be considered. Increased serum concentrations of carbamazepine were observed in clinical trials with clarithromycin. There have been spontaneous or published reports of CYP3A based interactions of clarithromycin with carbamazepine.
Antifungals:
Itraconazole | Use With Caution | Itraconazole: Both clarithromycin and itraconazole are substrates and inhibitors of CYP3A, potentially leading to a bi-directional drug interaction when administered concomitantly (see also Itraconazole under “Drugs That Affect Clarithromycin” in the table below). Clarithromycin may increase the plasma concentrations of itraconazole. Patients taking itraconazole and clarithromycin concomitantly should be monitored closely for signs or symptoms of increased or prolonged adverse reactions.
Fluconazole | No Dose Adjustment | Fluconazole: [see Pharmacokinetics (12.3)]
Anti-Gout Agents:
Colchicine (in patients with renal or hepatic impairment) | Contraindicated | Colchicine: Colchicine is a substrate for both CYP3A and the efflux transporter, P-glycoprotein (Pgp). Clarithromycin and other macrolides are known to inhibit CYP3A and Pgp. The dose of colchicine should be reduced when co-administered with clarithromycin in patients with normal renal and hepatic function [see Contraindications (4.4)and Warnings and Precautions (5.4)].
Colchicine (in patients with normal renal and hepatic function) | Use With Caution | Colchicine: Colchicine is a substrate for both CYP3A and the efflux transporter, P-glycoprotein (Pgp). Clarithromycin and other macrolides are known to inhibit CYP3A and Pgp. The dose of colchicine should be reduced when co-administered with clarithromycin in patients with normal renal and hepatic function [see Contraindications (4.4)and Warnings and Precautions (5.4)].
Antipsychotics:
Pimozide | Contraindicated | Pimozide: [See Contraindications (4.2)]
Quetiapine | Contraindicated | Quetiapine: Quetiapine is a substrate for CYP3A4, which is inhibited by clarithromycin. Co-administration with clarithromycin could result in increased quetiapine exposure and possible quetiapine related toxicities. There have been postmarketing reports of somnolence, orthostatic hypotension, altered state of consciousness, neuroleptic malignant syndrome, and QT prolongation during concomitant administration. Refer to quetiapine prescribing information for recommendations on dose reduction if co-administered with CYP3A4 inhibitors such as clarithromycin.
Lurasidone | Contraindicated | Lurasidone: [See Contraindications (4.7)]
Antispasmodics:
Tolterodine (patients deficient in CYP2D6 activity) | Use With Caution | Tolterodine: The primary route of metabolism for tolterodine is via CYP2D6. However, in a subset of the population devoid of CYP2D6, the identified pathway of metabolism is via CYP3A. In this population subset, inhibition of CYP3A results in significantly higher serum concentrations of tolterodine. Tolterodine 1 mg twice daily is recommended in patients deficient in CYP2D6 activity (poor metabolizers) when co-administered with clarithromycin.
Antivirals:
Atazanavir | Use With Caution | Atazanavir: Both clarithromycin and atazanavir are substrates and inhibitors of CYP3A, and there is evidence of a bi-directional drug interaction (see Atazanavir under “Drugs That Affect Clarithromycin”in the table below) [see Pharmacokinetics (12.3)].
Saquinavir (in patients with decreased renal function) |  | Saquinavir: Both clarithromycin and saquinavir are substrates and inhibitors of CYP3A and there is evidence of a bi-directional drug interaction (see Saquinavir under “Drugs That Affect Clarithromycin”in the table below) [ see Pharmacokinetics (12.3)].
Ritonavir Etravirine |  | Ritonavir, Etravirine:(see Ritonavir and Etravirine under “Drugs That Affect Clarithromycin”in the table below) [see Pharmacokinetics (12.3)].
Maraviroc |  | Maraviroc: Clarithromycin may result in increases in maraviroc exposures by inhibition of CYP3A metabolism. See Selzentry®prescribing information for dose recommendation when given with strong CYP3A inhibitors such as clarithromycin.
Boceprevir (in patients with normal renal function) Didanosine | No Dose Adjustment | Boceprevir: Both clarithromycin and boceprevir are substrates and inhibitors of CYP3A, potentially leading to a bi-directional drug interaction when co-administered. No dose adjustments are necessary for patients with normal renal function (see Victrelis® prescribing information).
Zidovudine |  | Zidovudine: Simultaneous oral administration of clarithromycin immediate-release tablets and zidovudine to HIV-infected adult patients may result in decreased steady-state zidovudine concentrations. Administration of clarithromycin and zidovudine should be separated by at least two hours [see Pharmacokinetics (12.3)] . The impact of co-administration of clarithromycin extended-release tablets or granules and zidovudine has not been evaluated.
Calcium Channel Blockers:
Verapamil | Use With Caution | Verapamil: Hypotension, bradyarrhythmias, and lactic acidosis have been observed in patients receiving concurrent verapamil, [see Warnings and Precautions (5.4)].
Amlodipine Diltiazem |  | Amlodipine, Diltiazem : [see Warnings and Precautions (5.4)]
Nifedipine |  | Nifedipine: Nifedipine is a substrate for CYP3A. Clarithromycin and other macrolides are known to inhibit CYP3A. There is potential of CYP3A-mediated interaction between nifedipine and clarithromycin. Hypotension and peripheral edema were observed when clarithromycin was taken concomitantly with nifedipine [see Warnings and Precautions (5.4)].
Ergot Alkaloids:
Ergotamine Dihydroergotamine | Contraindicated | Ergotamine, Dihydroergotamine: Postmarketing reports indicate that coadministration of clarithromycin with ergotamine or dihydroergotamine has been associated with acute ergot toxicity characterized by vasospasm and ischemia of the extremities and other tissues including the central nervous system [see Contraindications (4.6)].
Gastroprokinetic Agents:
Cisapride | Contraindicated | Cisapride: [See Contraindications (4.2)]
Lipid-lowering agents:
Lomitapide Lovastatin Simvastatin | Contraindicated | Lomitapide, Lovastatin, Simvastatin: Clarithromycin may increase the exposure of these drugs by inhibition of CYP3A metabolism, thereby increasing the risk of toxicities from these drugs [See Contraindications (4.5)and Warnings and Precautions (5.4)]
Atorvastatin Pravastatin | Use With Caution | Atorvastatin, Pravastatin, Fluvastatin : [See Warnings and Precautions (5.4)]
Fluvastatin | No Dose Adjustment
Hypoglycemic Agents:
Nateglinide Pioglitazone Repaglinide Rosiglitazone | Use With Caution | Nateglinide, Pioglitazone, Repaglinide, Rosiglitazone: [See Warnings and Precautions (5.4)and Adverse Reactions (6.2)]
Insulin |  | Insulin : [See Warnings and Precautions (5.4)and Adverse Reactions (6.2)]
Immunosuppressants:
Cyclosporine | Use With Caution | Cyclosporine: There have been spontaneous or published reports of CYP3A based interactions of clarithromycin with cyclosporine.
Tacrolimus |  | Tacrolimus: There have been spontaneous or published reports of CYP3A based interactions of clarithromycin with tacrolimus.
Phosphodiesterase inhibitors:
Sildenafil Tadalafil Vardenafil | Use With Caution | Sildenafil, Tadalafil, Vardenafil: Each of these phosphodiesterase inhibitors is primarily metabolized by CYP3A, and CYP3A will be inhibited by concomitant administration of clarithromycin. Co-administration of clarithromycin with sildenafil, tadalafil, or vardenafil will result in increased exposure of these phosphodiesterase inhibitors. Co-administration of these phosphodiesterase inhibitors with clarithromycin is not recommended. Increased systemic exposure of these drugs may occur with clarithromycin; reduction of dosage for phosphodiesterase inhibitors should be considered (see their respective prescribing information).
Proton Pump Inhibitors:
Omeprazole | No Dose Adjustment | Omeprazole: The mean 24-hour gastric pH value was 5.2 when omeprazole was administered alone and 5.7 when coadministered with clarithromycin as a result of increased omeprazole exposures [see Pharmacokinetics (12.3)] (see also Omeprazole under “Drugs That Affect Clarithromycin”in the table below).
Xanthine Derivatives:
Theophylline | Use With Caution | Theophylline: Clarithromycin use in patients who are receiving theophylline may be associated with an increase of serum theophylline concentrations [see Pharmacokinetics (12.3)] . Monitoring of serum theophylline concentrations should be considered for patients receiving high doses of theophylline or with baseline concentrations in the upper therapeutic range.
Triazolobenzodiazepines and Other Related Benzodiazepines:
Midazolam | Use With Caution | Midazolam: When oral midazolam is co-administered with clarithromycin, dose adjustments may be necessary and possible prolongation and intensity of effect should be anticipated [see Warnings and Precautions (5.4)and Pharmacokinetics (12.3)] .
Alprazolam Triazolam |  | Triazolam, Alprazolam: Caution and appropriate dose adjustments should be considered when triazolam or alprazolam is co-administered with clarithromycin. There have been postmarketing reports of drug interactions and central nervous system (CNS) effects (e.g., somnolence and confusion) with the concomitant use of clarithromycin and triazolam. Monitoring the patient for increased CNS pharmacological effects is suggested. In postmarketing experience, erythromycin has been reported to decrease the clearance of triazolam and midazolam, and thus, may increase the pharmacologic effect of these benzodiazepines.
Temazepam Nitrazepam Lorazepam | No Dose Adjustment | Temazepam, Nitrazepam, Lorazepam: For benzodiazepines which are not metabolized by CYP3A (e.g., temazepam, nitrazepam, lorazepam), a clinically important interaction with clarithromycin is unlikely.
Cytochrome P450 Inducers:
Rifabutin | Use With Caution | Rifabutin: Concomitant administration of rifabutin and clarithromycin resulted in an increase in rifabutin, and decrease in clarithromycin serum levels together with an increased risk of uveitis (see Rifabutin under “Drugs That Affect Clarithromycin”in the table below).
Other Drugs Metabolized by CYP3A:
Alfentanil Bromocriptine Cilostazol Methylprednisole Vinblastine Phenobarbital St. John’s Wort | Use With Caution | There have been spontaneous or published reports of CYP3A based interactions of clarithromycin with alfentanil, methylprednisolone, cilostazol, bromocriptine, vinblastine, phenobarbital, and St. John’s Wort.
Other Drugs Metabolized by CYP450 Isoforms Other than CYP3A:
Hexobarbital Phenytoin Valproate | Use With Caution | There have been postmarketing reports of interactions of clarithromycin with drugs not thought to be metabolized by CYP3A, including hexobarbital, phenytoin, and valproate.
Drugs that Affect Clarithromycin
Drug(s) that Affect the Pharmacokinetics of Clarithromycin | Recommendation | Comments
Antifungals:
Itraconazole | Use With Caution | Itraconazole: Itraconazole may increase the plasma concentrations of clarithromycin. Patients taking itraconazole and clarithromycin concomitantly should be monitored closely for signs or symptoms of increased or prolonged adverse reactions (see also Itraconazole under “Drugs That Are Affected By Clarithromycin”in the table above).
Antivirals:
Atazanavir | Use With Caution | Atazanavir: When clarithromycin is co-administered with atazanavir, the dose of clarithromycin should be decreased by 50% [see Clinical Pharmacology (12.3)]. Since concentrations of 14-OH clarithromycin are significantly reduced when clarithromycin is co-administered with atazanavir, alternative antibacterial therapy should be considered for indications other than infections due to Mycobacterium aviumcomplex. Doses of clarithromycin greater than 1000 mg per day should not be co-administered with protease inhibitors.
Ritonavir (in patients with decreased renal function) |  | Ritonavir: Since concentrations of 14-OH clarithromycin are significantly reduced when clarithromycin is co-administered with ritonavir, alternative antibacterial therapy should be considered for indications other than infections due to Mycobacterium avium [see Pharmacokinetics (12.3)]. Doses of clarithromycin greater than 1000 mg per day should not be co-administered with protease inhibitors.
Saquinavir (in patients with decreased renal function) |  | Saquinavir: When saquinavir is co-administered with ritonavir, consideration should be given to the potential effects of ritonavir on clarithromycin (refer to ritonavir above) [see Pharmacokinetics (12.3)].
Etravirine |  | Etravirine: Clarithromycin exposure was decreased by etravirine; however, concentrations of the active metabolite, 14-OH-clarithromycin, were increased. Because 14-OH-clarithromycin has reduced activity against Mycobacterium aviumcomplex (MAC), overall activity against this pathogen may be altered; therefore alternatives to clarithromycin should be considered for the treatment of MAC.
Saquinavir (in patients with normal renal function) | No Dose Adjustment
Ritonavir (in patients with normal renal function)
Proton Pump Inhibitors:
Omeprazole | Use With Caution | Omeprazole: Clarithromycin concentrations in the gastric tissue and mucus were also increased by concomitant administration of omeprazole [see Pharmacokinetics (12.3)].
Miscellaneous Cytochrome P450 Inducers:
Efavirenz Nevirapine Rifampicin Rifabutin Rifapentine | Use With Caution | Inducers of CYP3A enzymes, such as efavirenz, nevirapine, rifampicin, rifabutin, and rifapentine will increase the metabolism of clarithromycin, thus decreasing plasma concentrations of clarithromycin, while increasing those of 14-OH-clarithromycin. Since the microbiological activities of clarithromycin and 14-OH-clarithromycin are different for different bacteria, the intended therapeutic effect could be impaired during concomitant administration of clarithromycin and enzyme inducers. Alternative antibacterial treatment should be considered when treating patients receiving inducers of CYP3A. There have been spontaneous or published reports of CYP3A based interactions of clarithromycin with rifabutin (see Rifabutin under “Drugs That Are Affected By Clarithromycin”in the table above).

8 USE IN SPECIFIC POPULATIONS

8.1 Pregnancy

Risk Summary

Based on findings from animal studies, clarithromycin is not recommended for use in pregnant women except in clinical circumstances where no alternative therapy is appropriate. If pregnancy occurs while taking clarithromycin, the patient should be apprised of the potential hazard to the fetus [see Warnings and Precautions (5.7)].

Limited data from a small number of published human studies with clarithromycin use during pregnancy are insufficient to inform drug-associated risks of major birth defects, miscarriage, or adverse maternal or fetal outcomes. In animal reproduction studies, administration of oral clarithromycin to pregnant mice, rats, rabbits, and monkeys during the period of organogenesis produced malformations in rats (cardiovascular anomalies) and mice (cleft palate) at clinically relevant doses based on body surface area comparison. Fetal effects in mice, rats, and monkeys (e.g., reduced fetal survival, body weight, body weight gain) and implantation losses in rabbits were generally considered to be secondary to maternal toxicity (see Data).

The estimated background risk of major birth defects and miscarriage for the indicated population is unknown. All pregnancies have a background risk of birth defect, loss, or other adverse outcomes. In the U.S. general population, the estimated background risk of major birth defects and miscarriage in clinically recognized pregnancies is 2% to 4% and 15% to 20%, respectively.

Data

Animal Data

Animal reproduction studies were conducted in mice, rats, rabbits, and monkeys with oral and intravenously administered clarithromycin. In pregnant mice, clarithromycin was administered during organogenesis (gestation day [GD] 6 to 15) at oral doses of 15, 60, 250, 500, or 1000 mg/kg/day. Reduced body weight observed in dams at 1000 mg/kg/day (3 times the maximum recommended human dose [MRHD] based on body surface area comparison) resulted in reduced survival and body weight of the fetuses. At ≥ 500 mg/kg/day, increases in the incidence of post-implantation loss and cleft palate in the fetuses were observed. No adverse developmental effects were observed in mice at ≤ 250 mg/kg/day (≤ 1 times MRHD based on body surface area comparison).

In pregnant Sprague Dawley rats, clarithromycin was administered during organogenesis (GD 6 to 15) at oral doses of 15, 50, or 150 mg/kg/day. Reductions in body weight and food consumption was observed in dams at 150 mg/kg/day. Increased resorptions and reduced body weight of the fetuses at this dose were considered secondary to maternal toxicity. Additionally, at 150 mg/kg/day (1 times MRHD based on body surface area comparison), a low incidence of cardiovascular anomalies (complete situs inversus, undivided truncus, IV septal defect) was observed in the fetuses. Clarithromycin did not cause adverse developmental effects in rats at 50 mg/kg/day (0.3 times MRHD based on body surface area comparison). Intravenous dosing of clarithromycin during organogenesis in rats (GD 6 to 15) at 15, 50, or 160 mg/kg/day was associated with maternal toxicity (reduced body weight, body-weight gain, and food consumption) at 160 mg/kg/day but no evidence of adverse developmental effects at any dose (≤ 1 times MRHD based on body surface area comparison).

In pregnant Wistar rat, clarithromycin was administered during organogenesis (GD 7 to 17) at oral doses of 10, 40, or 160 mg/kg/day. Reduced body weight and food consumption were observed in dams at 160 mg/kg/day but there was no evidence of adverse developmental effects at any dose (≤ 1 times MRHD based on body surface area comparison).

In pregnant rabbits, clarithromycin administered during organogenesis (GD 6 to 18) at oral doses of 10, 35, or 125 mg/kg/day resulted in reduced maternal food consumption and decreased body weight at the highest dose, with no evidence of any adverse developmental effects at any dose (≤ 2 times MRHD based on body surface area comparison). Intravenously administered clarithromycin to pregnant rabbits during organogenesis (GD 6 to 18) in rabbits at 20, 40, 80, or 160 mg/kg/day (≥ 0.3 times MRHD based on body surface area comparison) resulted in maternal toxicity and implantation losses at all doses.

In pregnant monkeys, clarithromycin was administered (GD 20 to 50) at oral doses of 35 or 70 mg/kg/day. Dose-dependent emesis, poor appetite, fecal changes, and reduced body weight were observed in dams at all doses (≥ 0.5 times MRHD based on body surface area comparison).

Growth retardation in 1 fetus at 70 mg/kg/day was considered secondary to maternal toxicity. There was no evidence of primary drug related adverse developmental effects at any dose tested.

In a reproductive toxicology study in rats administered oral clarithromycin late in gestation through lactation (GD 17 to post-natal day 21) at doses of 10, 40, or 160 mg/kg/day (≤ 1 times MRHD based on body surface area comparison), reductions in maternal body weight and food consumption were observed at 160 mg/kg/day. Reduced body-weight gain observed in offspring at 160 mg/kg/day was considered secondary to maternal toxicity. No adverse developmental effects were observed with clarithromycin at any dose tested.

8.2 Lactation

Risk Summary

Based on limited human data, clarithromycin and its active metabolite 14-OH clarithromycin are present in human milk at less than 2% of the maternal weight-adjusted dose (see Data). In a separate observational study, reported adverse effects on breast-fed children (rash, diarrhea, loss of appetite, somnolence) were comparable to amoxicillin (see Data). No data are available to assess the effects of clarithromycin or 14-OH clarithromycin on milk production.

The development and health benefits of breastfeeding should be considered along with the mother’s clinical need for clarithromycin and any potential adverse effects on the breast-fed child from clarithromycin or from the underlying maternal condition.

Data

Human

Serum and milk samples were obtained after 3 days of treatment, at steady state, from one published study of 12 lactating women who were taking clarithromycin 250 mg orally twice daily. Based on the limited data from this study, and assuming milk consumption of 150 mL/kg/day, an exclusively human milk fed infant would receive an estimated average of 136 mcg/kg/day of clarithromycin and its active metabolite, with this maternal dosage regimen. This is less than 2% of the maternal weight-adjusted dose (7.8 mg/kg/day, based on the average maternal weight of 64 kg), and less than 1% of the pediatric dose (15 mg/kg/day) for children greater than 6 months of age.

A prospective observational study of 55 breastfed infants of mothers taking a macrolide antibacterial (6 were exposed to clarithromycin) were compared to 36 breastfed infants of mothers taking amoxicillin. Adverse reactions were comparable in both groups. Adverse reactions occurred in 12.7% of infants exposed to macrolides and included rash, diarrhea, loss of appetite, and somnolence.

8.3 Females and Males of Reproductive Potential

Males

Administration of clarithromycin resulted in testicular atrophy in rats, dogs and monkeys [see Nonclinical Toxicology (13.1)].

8.4 Pediatric Use

The safety and effectiveness of clarithromycin extended-release tablets in the treatment of pediatric patients has not been established.

Safety and effectiveness of clarithromycin in pediatric patients under 6 months of age have not been established. The safety of clarithromycin has not been studied in MAC patients under the age of 20 months.

8.5 Geriatric Use

In a steady-state study in which healthy elderly subjects (65 years to 81 years of age) were given 500 mg of clarithromycin every 12 hours, the maximum serum concentrations and area under the curves of clarithromycin and 14-OH clarithromycin were increased compared to those achieved in healthy young adults. These changes in pharmacokinetics parallel known age-related decreases in renal function. In clinical trials, elderly patients did not have an increased incidence of adverse reactions when compared to younger patients. Consider dosage adjustment in elderly patients with severe renal impairment. Elderly patients may be more susceptible to development of torsades de pointesarrhythmias than younger patients [see Warnings and Precautions (5.3)].

Most reports of acute kidney injury with calcium channel blockers metabolized by CYP3A4 (e.g., verapamil, amlodipine, diltiazem, nifedipine) involved elderly patients 65 years of age or older [see Warnings and Precautions (5.4)].

Especially in elderly patients, there have been reports of colchicine toxicity with concomitant use of clarithromycin and colchicine, some of which occurred in patients with renal insufficiency. Deaths have been reported in some patients [see Contraindications (4.4)and Warnings and Precautions (5.4)] .

8.6 Renal and Hepatic Impairment

Clarithromycin is principally excreted via the liver and kidney. Clarithromycin may be administered without dosage adjustment to patients with hepatic impairment and normal renal function. However, in the presence of severe renal impairment with or without coexisting hepatic impairment, decreased dosage or prolonged dosing intervals may be appropriate [see Dosage and Administration (2.6)].

10 OVERDOSAGE

Overdosage of clarithromycin can cause gastrointestinal symptoms such as abdominal pain, vomiting, nausea, and diarrhea.

Treat adverse reactions accompanying overdosage by the prompt elimination of unabsorbed drug and supportive measures. As with other macrolides, clarithromycin serum concentrations are not expected to be appreciably affected by hemodialysis or peritoneal dialysis.

11 DESCRIPTION

Clarithromycin is a semi-synthetic macrolide antimicrobial for oral use. Chemically, it is 6- 0-methylerythromycin. The molecular formula is C38H69NO13, and the molecular weight is 747.96. The structural formula is:

Figure 1: Structure of Clarithromycin

Clarithromycin is a white to off-white crystalline powder. It is soluble in acetone, slightly soluble in methanol, ethanol, and acetonitrile, and practically insoluble in water.

Clarithromycin is available as extended-release tablets.

Each white or off-white, capsular-shaped film-coated Clarithromycin Extended-Release Tablets, USP contains 500 mg of clarithromycin and the following inactive ingredients: glyceryl dibehenate, hypromellose, lactose monohydrate, magnesium stearate, polyethylene glycol, and titanium dioxide.

Clarithromycin Extended-Release Tablets, USP meets the dissolution specifications which were established according to the USP monograph-clarithromycin extended-release tablets Test 2.

12 CLINICAL PHARMACOLOGY

12.1 Mechanism of Action

Clarithromycin is a macrolide antimicrobial drug [see Microbiology (12.4)].

12.3 Pharmacokinetics

Absorption

Clarithromycin Extended-Release Tablets

Clarithromycin extended-release tablets provide extended absorption of clarithromycin from the gastrointestinal tract after oral administration. Relative to an equal total daily dose of immediate-release clarithromycin tablets, clarithromycin extended-release tablets provide lower and later steady-state peak plasma concentrations but equivalent 24-hour AUCs for both clarithromycin and its microbiologically-active metabolite, 14-OH clarithromycin. While the extent of formation of 14-OH clarithromycin following administration of clarithromycin extended-release tablets (2 x 500 mg tablets once daily) is not affected by food, administration under fasting conditions is associated with approximately 30% lower clarithromycin AUC relative to administration with food. Therefore, clarithromycin extended-release tablets should be taken with food.

Figure 2: Steady-State Clarithromycin Plasma Concentration-Time Profiles

Distribution

Clarithromycin and the 14-OH clarithromycin metabolite distribute readily into body tissues and fluids. There are no data available on cerebrospinal fluid penetration. Because of high intracellular concentrations, tissue concentrations are higher than serum concentrations. Examples of tissue and serum concentrations are presented below.

Table 9. Tissue and Serum Concentrations of Clarithromycin
CONCENTRATION (after 250 mg every 12 hours)
Tissue Type | Tissue (mcg/g) | Serum (mcg/mL)
Tonsil | 1.6 | 0.8
Lung | 8.8 | 1.7

Metabolism and Elimination

Clarithromycin Extended-Release Tablets

In healthy human subjects, steady-state peak plasma clarithromycin concentrations of approximately 2 mcg/mL to 3 mcg/mL were achieved about 5 hours to 8 hours after oral administration of 1000 mg clarithromycin extended-release tablets once daily; for 14-OH clarithromycin, steady-state peak plasma concentrations of approximately 0.8 mcg/mL were attained about 6 hours to 9 hours after dosing. Steady-state peak plasma clarithromycin concentrations of approximately 1 mcg/mL to 2 mcg/mL were achieved about 5 hours to 6 hours after oral administration of a single 500 mg clarithromycin extended-release tablets once daily; for 14-OH clarithromycin, steady-state peak plasma concentrations of approximately 0.6 mcg/mL were attained about 6 hours after dosing.

Steady-state peak plasma concentrations were attained in 2 days to 3 days and were approximately 2 mcg/mL for clarithromycin and 0.7 mcg/mL for 14-OH clarithromycin when 250-mg doses of the clarithromycin suspension were administered every 12 hours. Elimination half-life of clarithromycin (3 hours to 4 hours) and that of 14-OH clarithromycin (5 hours to 7 hours) were similar to those observed at steady state following administration of equivalent doses of clarithromycin immediate-release tablets.

Specific Populations for clarithromycin extended-release tablets

HIV Infection

Steady-state concentrations of clarithromycin and 14-OH clarithromycin observed following administration of 500 mg doses of clarithromycin every 12 hours to adult patients with HIV infection were similar to those observed in healthy volunteers. In adult HIV-infected patients taking 500-mg or 1000-mg doses of clarithromycin every 12 hours, steady-state clarithromycin Cmaxvalues ranged from 2 mcg/mL to 4 mcg/mL and 5 mcg/mL to 10 mcg/mL, respectively.

Hepatic Impairment

The steady-state concentrations of clarithromycin in subjects with impaired hepatic function did not differ from those in normal subjects; however, the 14-OH clarithromycin concentrations were lower in the hepatically impaired subjects. The decreased formation of 14-OH clarithromycin was at least partially offset by an increase in renal clearance of clarithromycin in the subjects with impaired hepatic function when compared to healthy subjects.

Renal Impairment

The pharmacokinetics of clarithromycin was also altered in subjects with impaired renal function [see Use in Specific Populations (8.6)and Dosage and Administration (2.6)].

Drug Interactions

Fluconazole

Following administration of fluconazole 200 mg daily and clarithromycin 500 mg twice daily to 21 healthy volunteers, the steady-state clarithromycin Cminand AUC increased 33% and 18%, respectively. Clarithromycin exposures were increased and steady-state concentrations of 14-OH clarithromycin were not significantly affected by concomitant administration of fluconazole.

Colchicine

When a single dose of colchicine 0.6 mg was administered with clarithromycin 250 mg BID for 7 days, the colchicine Cmaxincreased 197% and the AUC0-∞increased 239% compared to administration of colchicine alone.

Atazanavir

Following administration of clarithromycin (500 mg twice daily) with atazanavir (400 mg once daily), the clarithromycin AUC increased 94%, the 14-OH clarithromycin AUC decreased 70% and the atazanavir AUC increased 28%.

Ritonavir

Concomitant administration of clarithromycin and ritonavir (n = 22) resulted in a 77% increase in clarithromycin AUC and a 100% decrease in the AUC of 14-OH clarithromycin.

Saquinavir

Following administration of clarithromycin (500 mg bid) and saquinavir (soft gelatin capsules, 1200 mg tid) to 12 healthy volunteers, the steady-state saquinavir AUC and Cmaxincreased 177% and 187% respectively compared to administration of saquinavir alone. Clarithromycin AUC and Cmaxincreased 45% and 39% respectively, whereas the 14–OH clarithromycin AUC and Cmaxdecreased 24% and 34% respectively, compared to administration with clarithromycin alone.

Didanosine

Simultaneous administration of clarithromycin tablets and didanosine to 12 HIV-infected adult patients resulted in no statistically significant change in didanosine pharmacokinetics.

Zidovudine

Following administration of clarithromycin 500 mg tablets twice daily with zidovudine 100 mg every 4 hours, the steady-state zidovudine AUC decreased 12% compared to administration of zidovudine alone (n=4). Individual values ranged from a decrease of 34% to an increase of 14%. When clarithromycin tablets were administered two to four hours prior to zidovudine, the steady-state zidovudine Cmaxincreased 100% whereas the AUC was unaffected (n=24).

Omeprazole

Clarithromycin 500 mg every 8 hours was given in combination with omeprazole 40 mg daily to healthy adult subjects. The steady-state plasma concentrations of omeprazole were increased (Cmax, AUC0-24, and t½increases of 30%, 89%, and 34%, respectively), by the concomitant administration of clarithromycin.

The plasma levels of clarithromycin and 14–OH clarithromycin were increased by the concomitant administration of omeprazole. For clarithromycin, the mean Cmaxwas 10% greater, the mean Cminwas 27% greater, and the mean AUC0-8was 15% greater when clarithromycin was administered with omeprazole than when clarithromycin was administered alone. Similar results were seen for 14–OH clarithromycin, the mean Cmaxwas 45% greater, the mean Cminwas 57% greater, and the mean AUC0-8was 45% greater. Clarithromycin concentrations in the gastric tissue and mucus were also increased by concomitant administration of omeprazole.

Clarithromycin Tissue Concentrations 2 hours after Dose (mcg/mL)/(mcg/g)
Treatment | N | antrum | fundus | N | Mucus
Clarithromycin | 5 | 10.48 ± 2.01 | 20.81 ± 7.64 | 4 | 4.15 ± 7.74
Clarithromycin + Omeprazole | 5 | 19.96 ± 4.71 | 24.25 ± 6.37 | 4 | 39.29 ± 32.79

Theophylline

In two studies in which theophylline was administered with clarithromycin (a theophylline sustained-release formulation was dosed at either 6.5 mg/kg or 12 mg/kg together with 250 or 500 mg q12h clarithromycin), the steady-state levels of Cmax, Cmin, and the area under the serum concentration time curve (AUC) of theophylline increased about 20%.

Midazolam

When a single dose of midazolam was co-administered with clarithromycin tablets (500 mg twice daily for 7 days), midazolam AUC increased 174% after intravenous administration of midazolam and 600% after oral administration.

For information about other drugs indicated in combination with clarithromycin, refer to their full prescribing information, CLINICAL PHARMACOLOGYsection.

12.4 Microbiology

Mechanism of Action

Clarithromycin exerts its antibacterial action by binding to the 50S ribosomal subunit of susceptible bacteria resulting in inhibition of protein synthesis.

Resistance

The major routes of resistance are modification of the 23S rRNA in the 50S ribosomal subunit to insensitivity or drug efflux pumps. Beta-lactamase production should have no effect on clarithromycin activity.

Most isolates of methicillin-resistant and oxacillin-resistant staphylococci are resistant to clarithromycin.

Antimicrobial Activity

Clarithromycin has been shown to be active against most of the isolates of the following microorganisms both in vitroand in clinical infections [see Indications and Usage (1)].

Gram-Positive Bacteria

- Staphylococcus aureus
- Streptococcus pneumoniae
- Streptococcus pyogenes

Gram-Negative Bacteria

- Haemoph ilus influenzae
- Haemophilus parainfluenzae
- Moraxella catarrhalis

Other Microorganisms

- Chlamydophila pneumoniae
- Helicobacter pylori
- Mycobacterium avium complex (MAC) consisting of M. avium and M. intracellulare
- Mycoplasma pneumoniae

At least 90 percent of the microorganisms listed below exhibit in vitro minimum inhibitory concentrations (MICs) less than or equal to the clarithromycin susceptible MIC breakpoint for organisms of similar type to those shown in Table 11. However, the efficacy of clarithromycin in treating clinical infections due to these microorganisms has not been established in adequate and well-controlled clinical trials.

Gram-Positive Bacteria

- Streptococc us agalactiae
- Streptococci (Groups C, F, G)
- Viridans group streptococci

Gram-Negative Bacteria

- Legionella pneumophila
- Pasteurella multocida

Anaerobic Bacteria

- Clostridium perfringens
- Peptococcus niger
- Prevotella melaninogenica
- Propionibacterium acnes

Susceptibility Testing Methods (Excluding Mycobacteria and Helicobacter)

For specific information regarding susceptibility test interpretive criteria, and associated test methods and quality control standards recognized by FDA for this drug, please see: http://www.fda.gov/STIC.

13 NONCLINICAL TOXICOLOGY

13.1 Carcinogenesis, Mutagenesis, Impairment of Fertility

Mutagenesis

The following in vitro mutagenicity tests have been conducted with clarithromycin:

- Salmonella/Mammalian Microsomes Test
- Bacterial Induced Mutation Frequency Test
- In Vitro Chromosome Aberration Test
- Rat Hepatocyte DNA Synthesis Assay
- Mouse Lymphoma Assay
- Mouse Dominant Lethal Study
- Mouse Micronucleus Test

All tests had negative results except the in vitro chromosome aberration test which was positive in one test and negative in another. In addition, a bacterial reverse-mutation test (Ames test) has been performed on clarithromycin metabolites with negative results.

Impairment of Fertility

Fertility and reproduction studies have shown that daily doses of up to 160 mg/kg/day to male and female rats caused no adverse effects on the estrous cycle, fertility, parturition, or number and viability of offspring. Plasma levels in rats after 150 mg/kg/day were twice the human serum levels.

Testicular atrophy occurred in rats at doses 7 times, in dogs at doses 3 times, and in monkeys at doses 8 times greater than the maximum human daily dose (on a body surface area basis).

13.2 Animal Toxicology and/or Pharmacology

Corneal opacity occurred in dogs at doses 12 times and in monkeys at doses 8 times greater than the maximum human daily dose (on a body surface area basis). Lymphoid depletion occurred in dogs at doses 3 times greater than and in monkeys at doses 2 times greater than the maximum human daily dose (on a body surface area basis).

15 REFERENCES

1. Winkel P, Hilden J, Hansen JF, Kastrup J, Kolmos HJ, Kjøller E, et al. Clarithromycin for stable coronary heart disease increases all-cause and cardiovascular mortality and cerebrovascular morbidity over 10 years in the CLARICOR randomised, blinded clinical trial. Int J Cardiol 2015;182:459-65.
2. Kemper CA, et al. Treatment of Mycobacterium avium Complex Bacteremia in AIDS with a Four-Drug Oral Regimen. Ann Intern Med. 1992;116:466-472.

16 HOW SUPPLIED/STORAGE AND HANDLING

Clarithromycin Extended-Release Tablets, USP are supplied as white or off-white, capsular-shaped film-coated 500 mg tablets debossed “S58” on one side and blank on the other side.

500 mg tablets:

Bottles of 60 NDC 62135-883-60

Store clarithromycin extended-release tablets, USP at 20º to 25ºC (68º to 77ºF). [See USP Controlled Room Temperature].

17 PATIENT COUNSELING INFORMATION

Provide the following instructions or information about clarithromycin extended-release tablets to patients:

Important Administration Instructions

Advise patients that clarithromycin extended-release tablets should be taken with food.

Drug Interactions

Advise patients that clarithromycin may interact with some drugs; therefore, advise patients to report to their healthcare provider the use of any other medications.

Diarrhea

Advise patients that diarrhea is a common problem caused by antibacterials including clarithromycin which usually ends when the antibacterial is discontinued. Sometimes after starting treatment with antibacterials, patients can develop watery and bloody stools (with or without stomach cramps and fever) even as late as two or more months after having taken the last dose of the antibacterial. If this occurs, instruct patients to contact their healthcare provider as soon as possible.

Embryo-Fetal Toxicity

Advise females of reproductive potential that that if pregnancy occurs while taking this drug, there is a potential hazard to the fetus [see Warnings and Precautions (5.7)and Use in Specific Populations (8.1)].

Antibacterial Resistance

Counsel patients that antibacterial drugs including clarithromycin tablets should only be used to treat bacterial infections. They do not treat viral infections (e.g., the common cold). When clarithromycin tablet is prescribed to treat a bacterial infection, patients should be told that although it is common to feel better early in the course of therapy, the medication should be taken exactly as directed. Skipping doses or not completing the full course of therapy may (1) decrease the effectiveness of the immediate treatment and (2) increase the likelihood that bacteria will develop resistance and will not be treatable by clarithromycin tablets or other antibacterial drugs in the future.

Potential for Dizziness, Vertigo and Confusion

There are no data on the effect of clarithromycin on the ability to drive or use machines. However, counsel patients regarding the potential for dizziness, vertigo, confusion and disorientation, which may occur with the clarithromycin tablets. The potential for these adverse reactions should be taken into account before patients drive or use machines.

Risk of Mortality in Patients with Coronary Disease Years After clarithromycin Treatment

Advise patients who have coronary artery disease to continue medications and lifestyle modifications for their coronary artery disease because clarithromycin may be associated with increased risk for mortality years after the end of clarithromycin treatment.

* All trademark names are the property of their respective owners.

Manufactured by:

Sunshine Lake Pharma Co., Ltd.
No. 1, Northern Industry Road,
Northern Industry Park of Song Shan Lake
Dongguan 523808, Guangdong, China

Manufactured For:

Chartwell RX, LLC.

Congers, NY 10920

L72135
Rev. 04/2024

PRINCIPAL DISPLAY PANEL

Clarithromycin Extended-Release Tablets, USP 500 mg - NDC 62135-883-60 - 60s Bottle Label